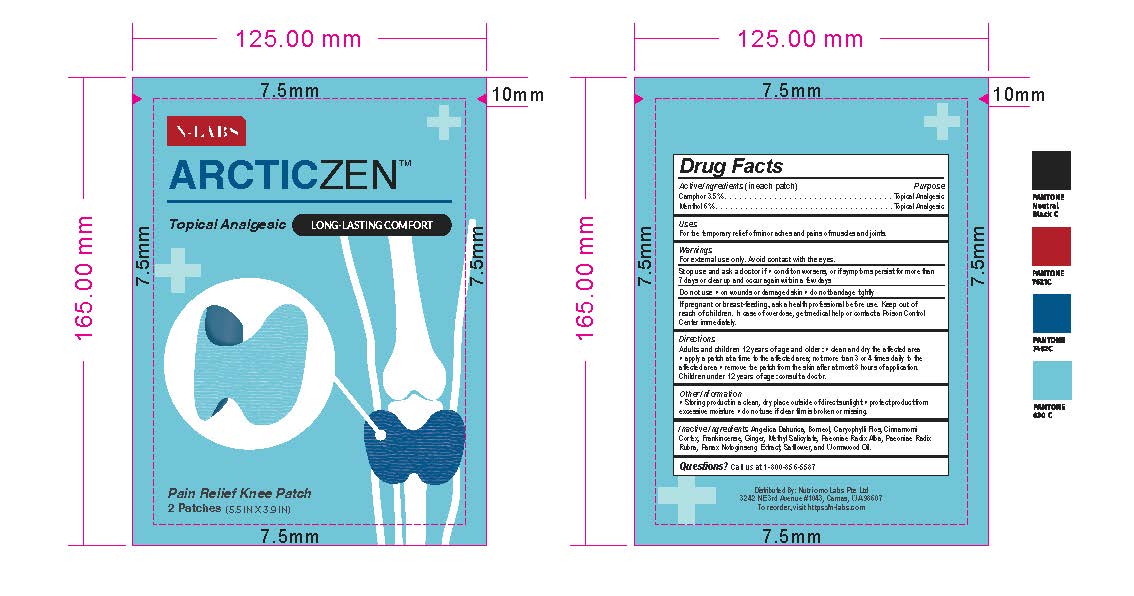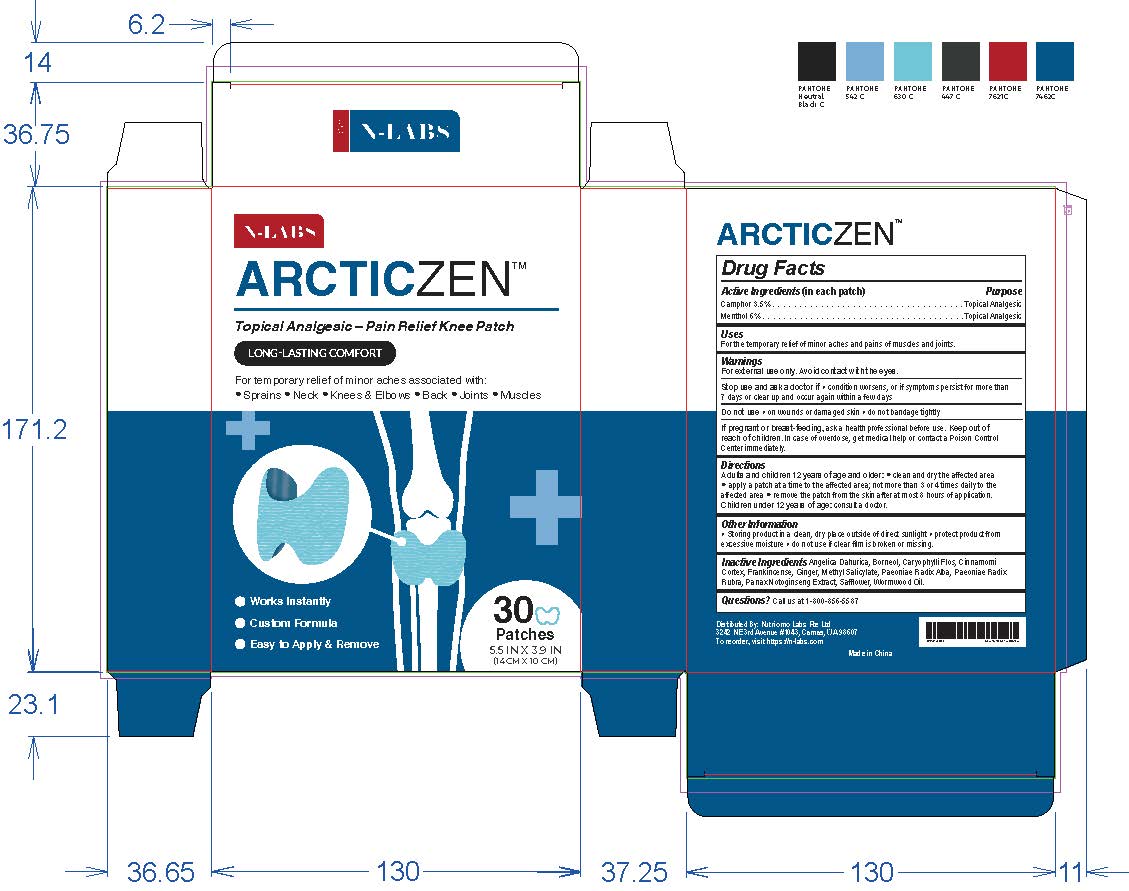 DRUG LABEL: N-Labs ArcticZen Pain Relief Knee
NDC: 71856-356 | Form: PATCH
Manufacturer: Nutriomo Labs PTE., LTD
Category: otc | Type: HUMAN OTC DRUG LABEL
Date: 20251227

ACTIVE INGREDIENTS: MENTHOL 60 mg/1 g; CAMPHOR (SYNTHETIC) 35 mg/1 g
INACTIVE INGREDIENTS: METHYL SALICYLATE; GINGER; WORMWOOD OIL; EUGENIA CARYOPHYLLUS (CLOVE) FLOWER OIL; AMORPHOPHALLUS PAEONIIFOLIUS ROOT; CINNAMOMUM CASSIA BARK OIL; PANAX NOTOGINSENG WHOLE; SAFFLOWER; FRANKINCENSE; ANGELICA DAHURICA ROOT; BORNEOL

ArcticZen Pain Relief Knee Patches
Update MFR and Label

Purpose

Topical Analgesic

Active Ingredients

Camphor 3.5%

Menthol 6%

Uses

For the temporary relief of minor aches and pains of muscles and joints.

Keep out of reach of children. In case of overdose, get medical help or contact a Poison Control
Center immediately.

Directions

Adults and children 12 years of age and older: ● clean and dry the affected area
● apply a patch at a time to the affected area; not more than 3 or 4 times daily to the
affected area ● remove the patch from the skin after at most 8 hours of application.
Children under 12 years of age: consult a doctor.

Warnings

For external use only. Avoid contact with the eyes.
Stop use and ask a doctor if ● condition worsens, or if symptoms persist for more than 7 days or clear up and occur again within a few days.
Do not use ● on wounds or damaged skin ● do not bandage tightly.
If pregnant or breast-feeding, ask a health professional before use

Inactive Ingredients

Angelica Dahurica, Borneol, Caryophylli Flos, Cinnamomi Cortex, Frankincense, Ginger, Methyl Salicylate, Paeoniae Radix Alba, Paeoniae Radix Rubra, Panax Notoginseng Extract, Safflower, and Wormwood Oil.

Other Information

● Storing product in a clean, dry place outside of direct sunlight ● protect product from
excessive moisture ● do not use if clear film is broken or missing.